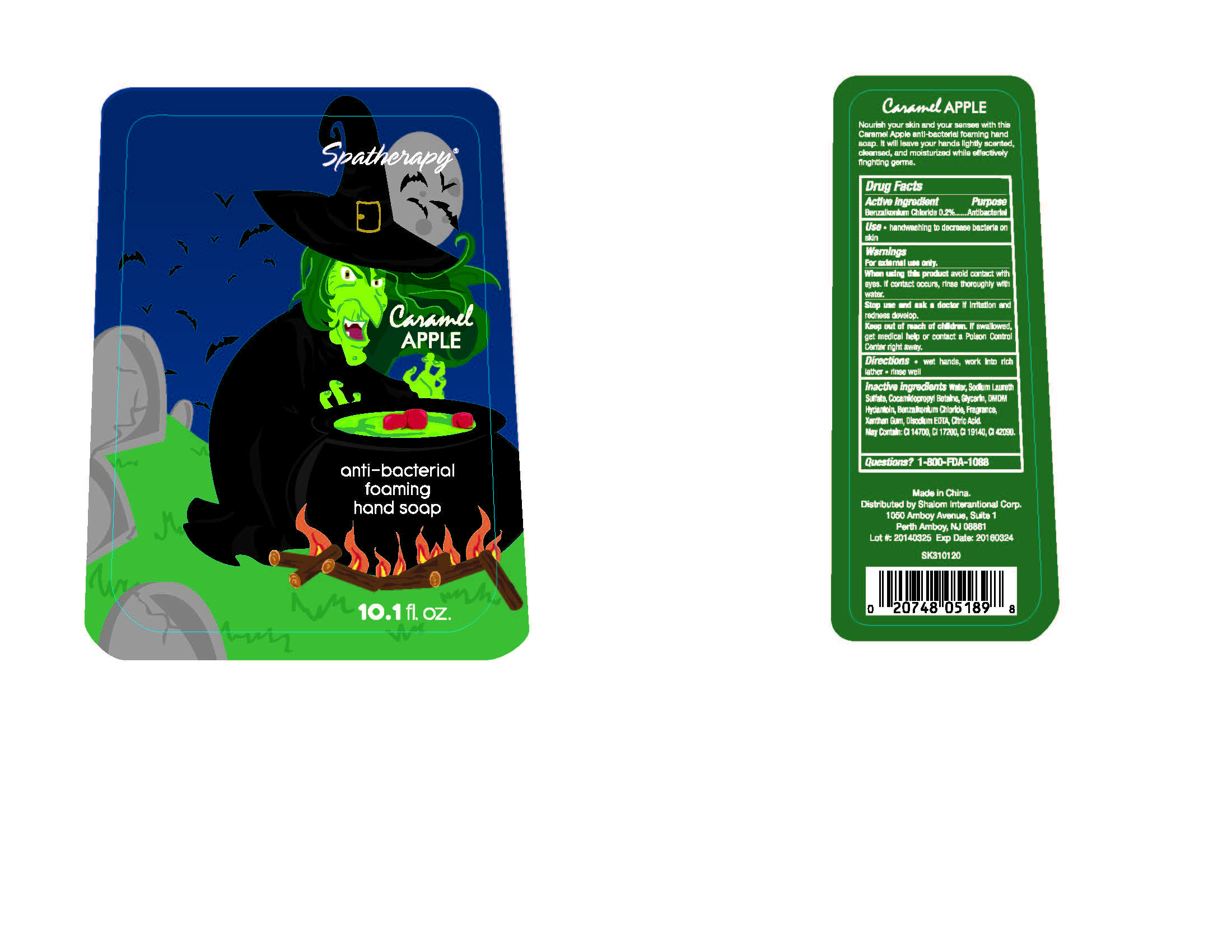 DRUG LABEL: Spatherapy
                
                
NDC: 56136-009 | Form: LOTION
Manufacturer: Xiamen Olivee Daily Use Chemical Co., Ltd.
Category: otc | Type: HUMAN OTC DRUG LABEL
Date: 20140407

ACTIVE INGREDIENTS: BENZALKONIUM CHLORIDE .56 g/293 g
INACTIVE INGREDIENTS: WATER; SODIUM LAURETH-3 SULFATE; COCAMIDOPROPYL BETAINE; GLYCERIN; DMDM HYDANTOIN; XANTHAN GUM; EDETATE DISODIUM; CITRIC ACID MONOHYDRATE; FD&C RED NO. 4; D&C RED NO. 33; FD&C YELLOW NO. 5; FD&C BLUE NO. 1

Drug Facts

Inactive Ingredients - Water, Sodium Laureth

Sulfate, Cocamidopropyl Betaine, Glycerin, DMDM

Hydantoin, Benalkonium Clhoride, Fragrance,

Xanthan Gum, Disodium EDTA,

Citiric Acid. May contain: CI 14700, CI 17200, CI 19140, Ci 42090

Active Ingredient

Benzalkonium Chloride 0,2 %

Purpose

Antibacterial

INDICATIONS AND USAGE

Use - handwashing to decrease bacteria on skin

DOSAGE AND ADMINISTRATION

Directions - wet hands, work into

rich lather - rinse well

Warnings

For external use only

When using this product, avoid contact with eyes. If contact occurs,

rinse thoroughly with water.

Stop use and ask a doctor if irritation and redness develop

KEEP OUT OF REACH OF CHILDREN

EKeep out of reach of children. If swallowed, get medical help

or contact a Poison Control Center right away.

Questions? 1-800-FDA-1088